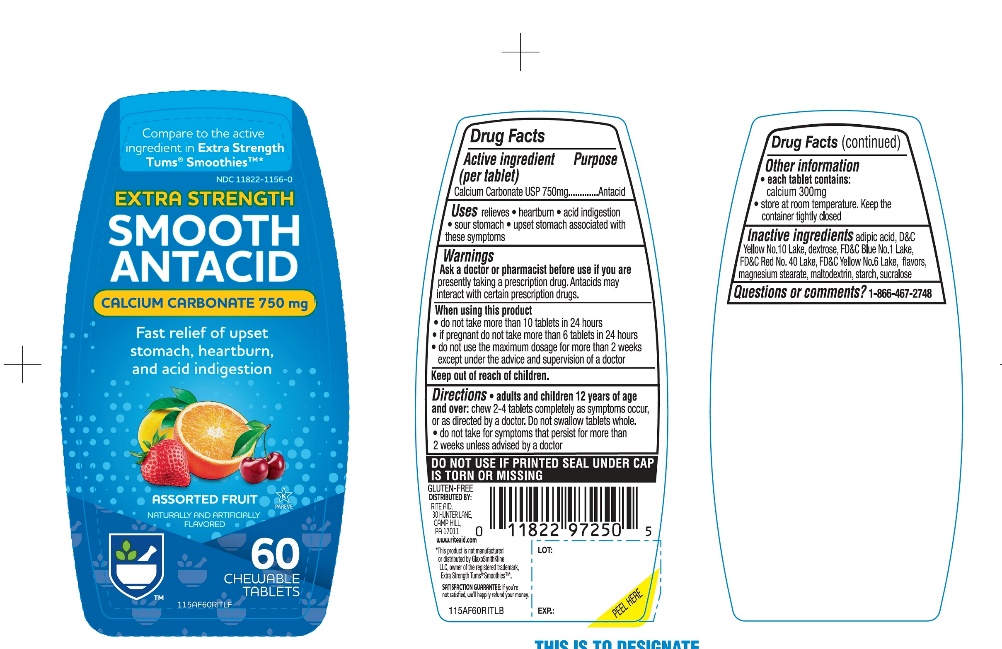 DRUG LABEL: Rite Aid Extra Strength
NDC: 11822-1156 | Form: TABLET, CHEWABLE
Manufacturer: RITE AID CORPORATION
Category: otc | Type: HUMAN OTC DRUG LABEL
Date: 20241030

ACTIVE INGREDIENTS: CALCIUM CARBONATE 750 mg/1 1
INACTIVE INGREDIENTS: ADIPIC ACID; D&C YELLOW NO. 10; DEXTROSE, UNSPECIFIED FORM; FD&C BLUE NO. 1; FD&C RED NO. 40; FD&C YELLOW NO. 6; MAGNESIUM STEARATE; MALTODEXTRIN; STARCH, CORN; SUCRALOSE

Rite Aid Extra Strength Smooth Antacid Assorted Fruit 60 Chewable Tablets

Active ingredient (per tablet)

Calcium Carbonate 750 mg

Purpose

Antacid

Uses

relieves:

- Heartburn
- acid indigestion
- sour stomach
- upset stomach associated with these symptoms

Ask a doctor or pharmacist before use if you are

- presently taking a prescription drug. Antacids may interact with certain prescription drugs.

When using this product

- do not take more than 10 tablets in a 24-hours
- if pregnant do not take more than 6 tablets in 24 hours
- do not use the maximum dosage for more than 2 weeks except under the advice and supervision of a doctor.

Directions

- adults and children 12 years of age and over: chew 2-4 tablets as symptoms occur, or as directed by a doctor.
- do not take for symptoms that persists for more than 2 weeks unless advised by a doctor

Other information

- each tablet contains: elemental calcium 300 mg
- Store at room temperature. keep the container tightly closed.

Safety sealed: Do not use if printed seal under cap is torn or missing

Inactive ingredients

adipic acid, D&C Yellow No. 10, dextrose, FD&C Blue No. 1, FD&C Red No. 40, FD&C Yellow No. 6, flavors, magnesium stearate, maltodextrin, starch, sucralose.

Questions or comments

1-866-467-2748

PRINCIPAL DISPLAY PANEL

RITE AID®

PHARMACY

NDC 11822-1156-0

*Compare to the active ingredient in Extra Strength Tums® Smoothies TM *

EXTRA STRENGTH

SMOOTH ANTACID

CALCIUM CARBONATE 750 mg

ASSORTED FRUIT FLAVORS

NATURALLY AND ARTIFICIALLY FLAVORED

Fast relief of upset stomach, heartburn and acid indigestion

60 CHEWABLE TABLETS

K PAREVE

GLUTEN-FREE
DISTRIBUTED. BY: RITE AID 30 HUNTER LANE,

CAMP HILL, PA 17011

This product is not manufactured or distributed by GlaxoSmithKline LLC, owner of the registered trademark, Extra Strength Tums® Smoothies TM *.

SATISFACTION GUARANTEE

if you are not satisfied, we’ll happily refund your money.